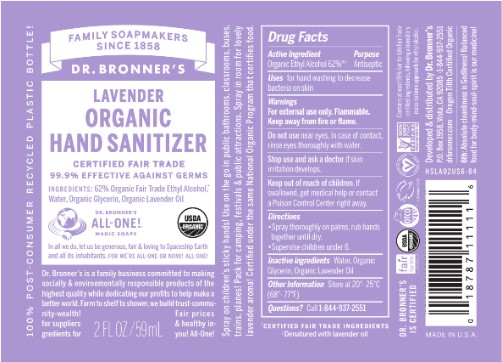 DRUG LABEL: Dr Bronners
NDC: 73333-161 | Form: SPRAY
Manufacturer: Nutrix International, LLC.
Category: otc | Type: HUMAN OTC DRUG LABEL
Date: 20220510

ACTIVE INGREDIENTS: ALCOHOL 0.7 g/59 g
INACTIVE INGREDIENTS: GLYCERIN 0.01 g/59 g; LAVENDER OIL 0.0022 g/59 g; WATER 0.2878 g/59 g

Dr Bronner's Hand Sanitizer Lavander

ACTIVE INGREDIENT

ACTIVE INGREDIENTS:ETHYL ALCOHOL 62%

PURPOSE

ANTISEPTIC

INDICATIONS & USAGE

USES: FOR HAND WASHING TO DECREASE BACTERIA ON SKIN.

WARNINGS

FOR EXTERNAL USE ONLY. FLAMMABLE, KEEP AWAY FROM FIRE OR FLAME.

INACTIVE INGREDIENT

WATER, GLYCERIN, LAVENDER OIL

KEEP OUT OF REACH OF CHILDREN. IF SWALLOWED, GET MEDICAL HELP OR CONTACT A POISON CONTROL CENTER RIGHT AWAY.

DO NOT USE IN THE EYES. IN CASE OF CONTACT, RINSE EYES THOROUGHLY WITH WATER.

STOP USE

STOP USE AND ASK A DOCTOR IF IRRITATION AND REDNESS DEVELOP AND PERSIST FOR MORE THAN 72 HRS.

DOSAGE & ADMINISTRATION

SPRAY ON PALM, RUB HANDS TOGETHER. SUPERVISE CHILDREN.

QUESTIONS

QUESTIONS? CALL 760-743-2211

DISPLAY PANEL

LABEL